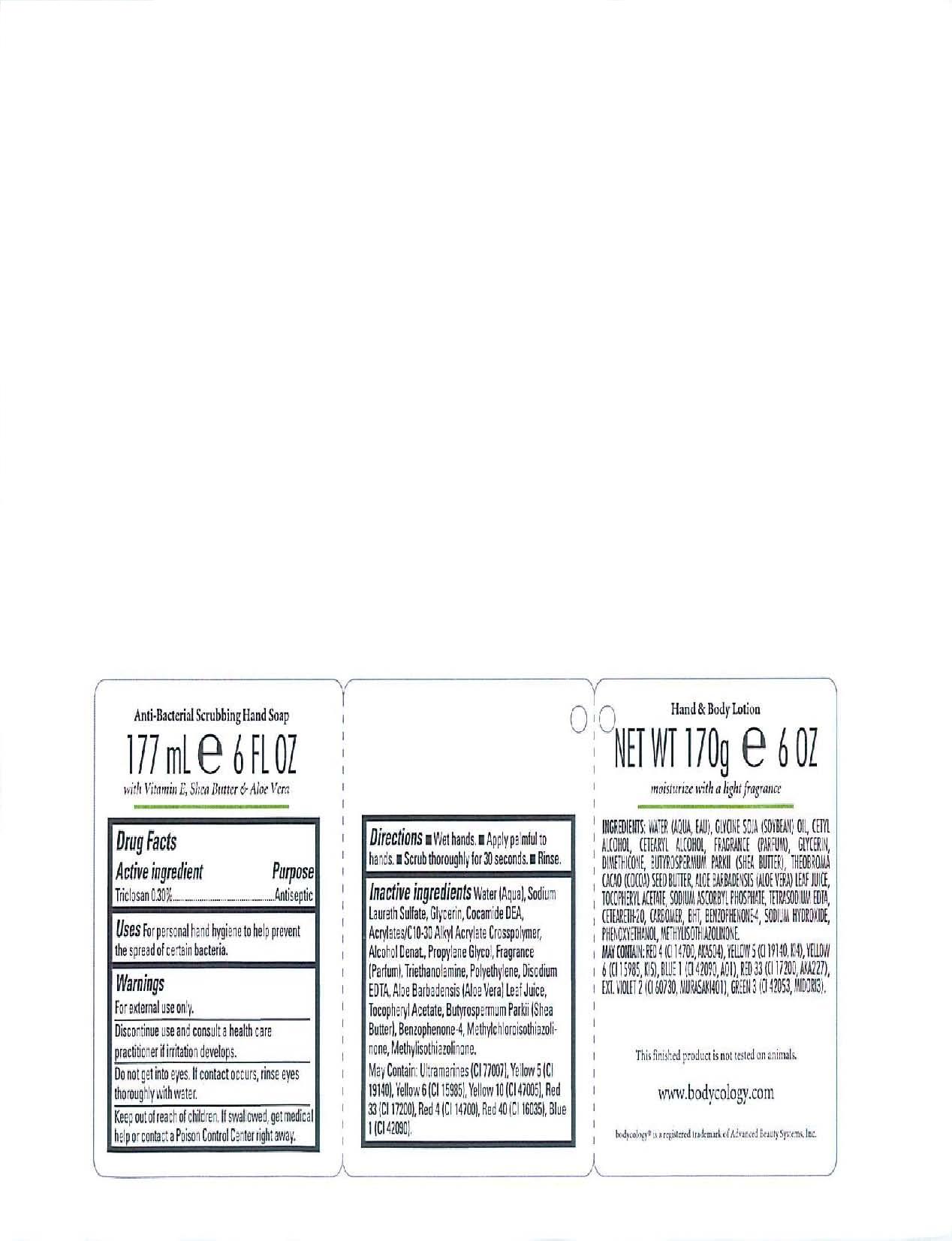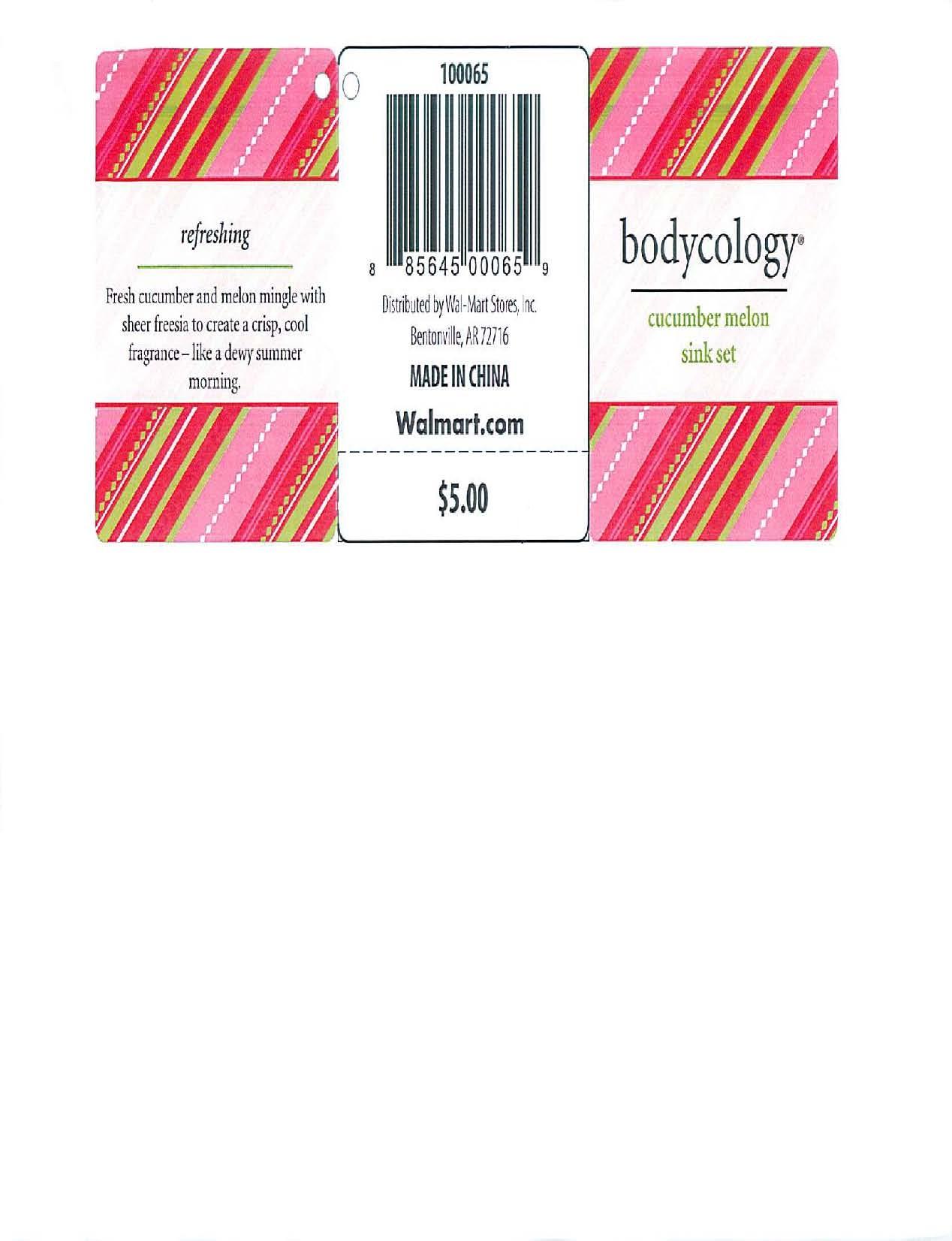 DRUG LABEL: Bodycology
NDC: 51706-114 | Form: GEL
Manufacturer: Landy International
Category: otc | Type: HUMAN OTC DRUG LABEL
Date: 20100628

ACTIVE INGREDIENTS: TRICLOSAN 0.30 mL/100 mL

Cucumber Melon Sink Set

Active Ingredients Purpose

Triclosan 0.30% Antiseptic

Warnings:

-For external use only.

-discontinue use and consult a health care practitioner if irritation develops

-do not get into eyes. If contact occurs, rinse eyes thoroughly with water

-Keep out of reach of children. If swallowed, get medical help or contact a Poison Control Center right away.

INDICATIONS AND USAGE

Uses: for personal hand hygiene to help prevent the spread of certain bacteria

Directions: wet hands, apply palmful to hands, scrub thoroughly for 30 seconds, rinse.

INACTIVE INGREDIENT

Inactive Ingredients: Water (Aqua), Sodium Laureth Sulfate, Glycerin, Cocamide DEA, Acrylates/C10-30 Alkyl Acrylate Crosspolymer, Alcohol Denat., Propylene Glycol, Fragrance (Parfum), Triethanolamine, Polyethylene, Disodium EDTA, Aloe Barbadensis (Aloe Vera) Leaf Juice, Tocopheryl Acetate, Butyrospermum Parkii (Shea Butter), Benzophenone-4, Methylchloroisothiazolinone, Methylisothiazolinone. May Contain: Ultramarines (CI 77007), Yellow 5 (CI 19140), Yellow 6 (CI 15985), Yellow 10 (CI 47005), Red 33 (CI 17200), Red 4 (CI 14700), Red 40 (CI 16035), Blue 1 (CI 42090)

PACKAGE LABEL

Anti-Bacterial Scrubbing Hand Soap

177ml/6 fl. oz.